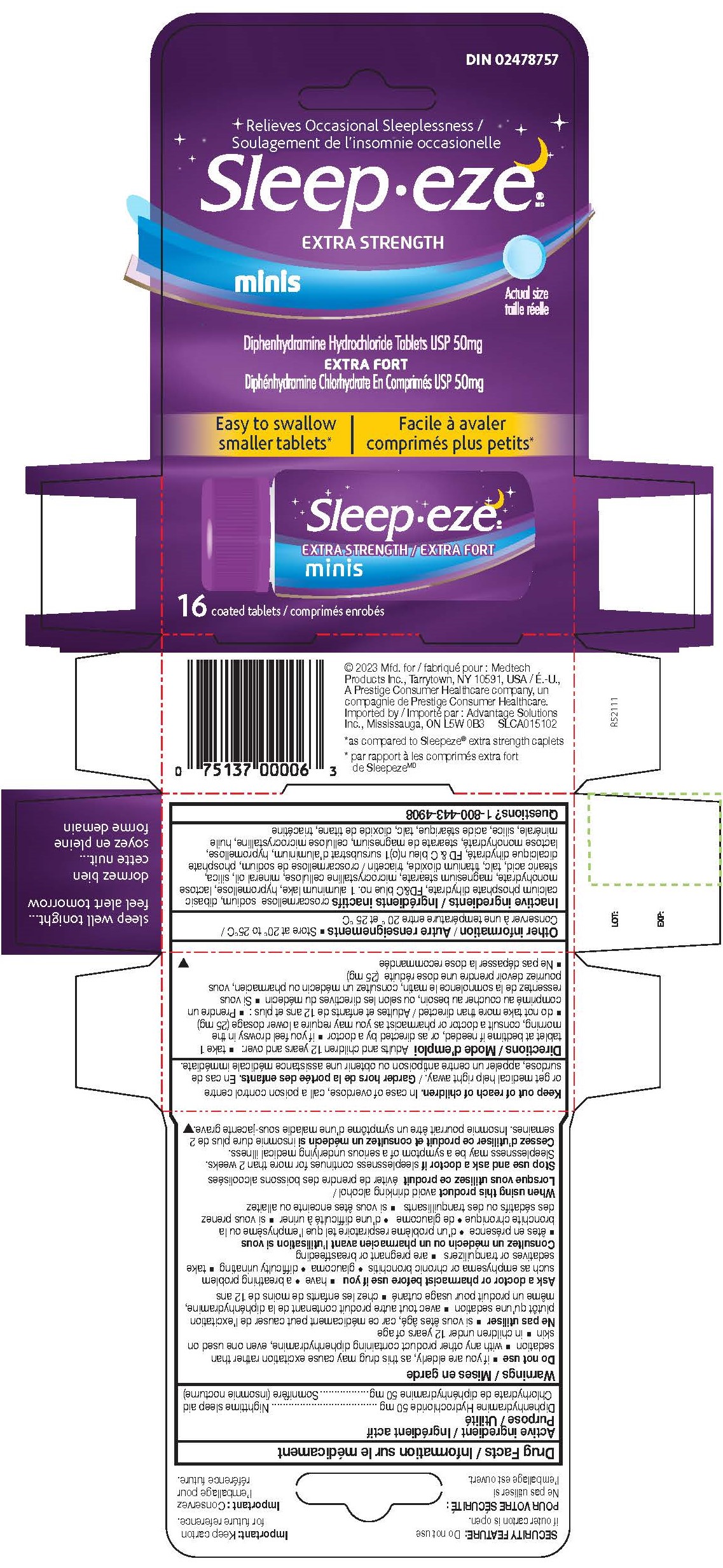 DRUG LABEL: Diphenhydramine Hydrochloride
NDC: 10267-5344 | Form: TABLET, FILM COATED
Manufacturer: Contract Pharmacal Corp.
Category: otc | Type: HUMAN OTC DRUG LABEL
Date: 20231201

ACTIVE INGREDIENTS: DIPHENHYDRAMINE HYDROCHLORIDE 50 mg/1 1
INACTIVE INGREDIENTS: SILICON DIOXIDE; HYPROMELLOSES; TALC; CROSCARMELLOSE SODIUM; FD&C BLUE NO. 1; LACTOSE MONOHYDRATE; MAGNESIUM STEARATE; MICROCRYSTALLINE CELLULOSE; LIGHT MINERAL OIL; STEARIC ACID; TITANIUM DIOXIDE; TRIACETIN; DIBASIC CALCIUM PHOSPHATE DIHYDRATE

5344- Export